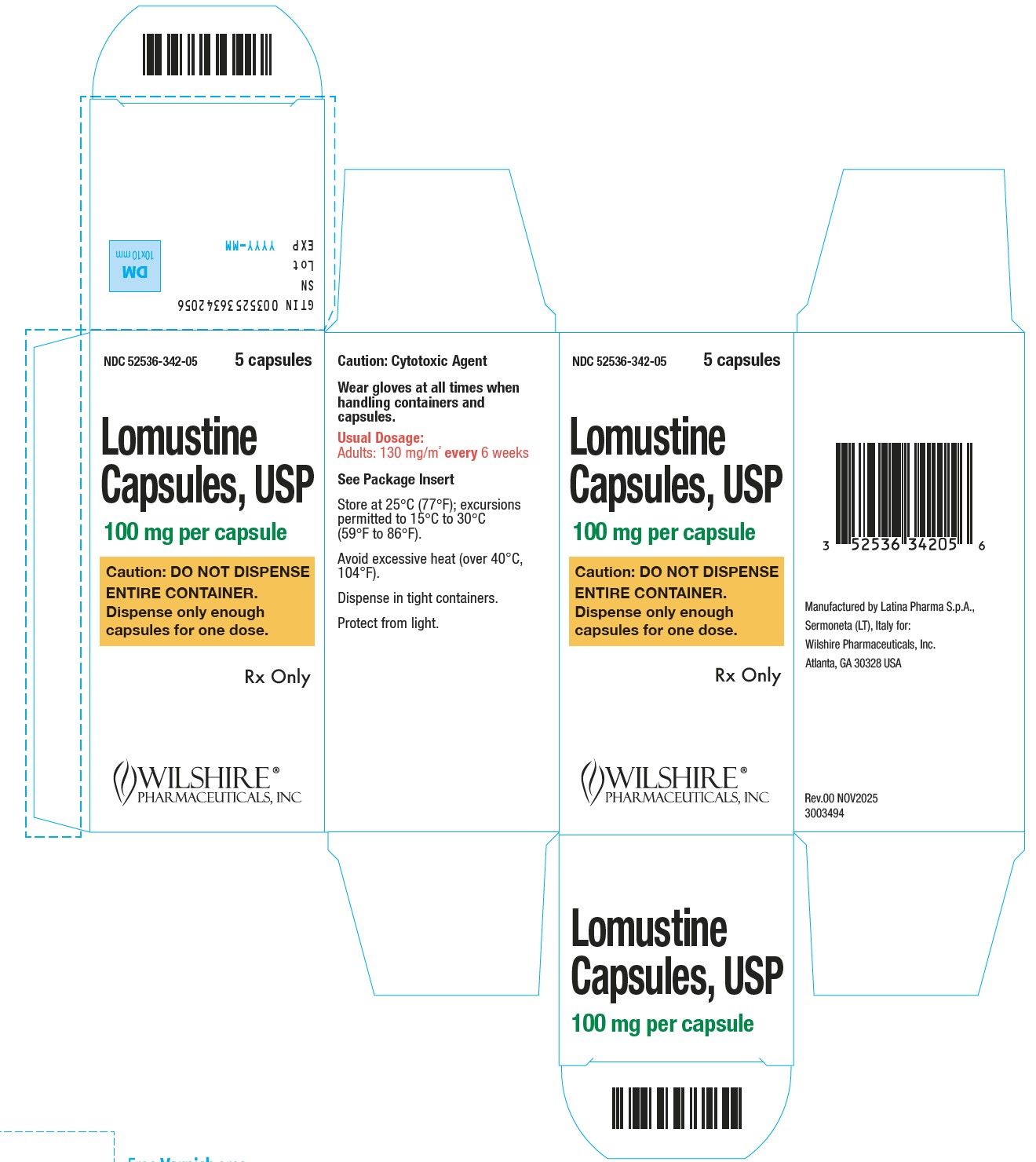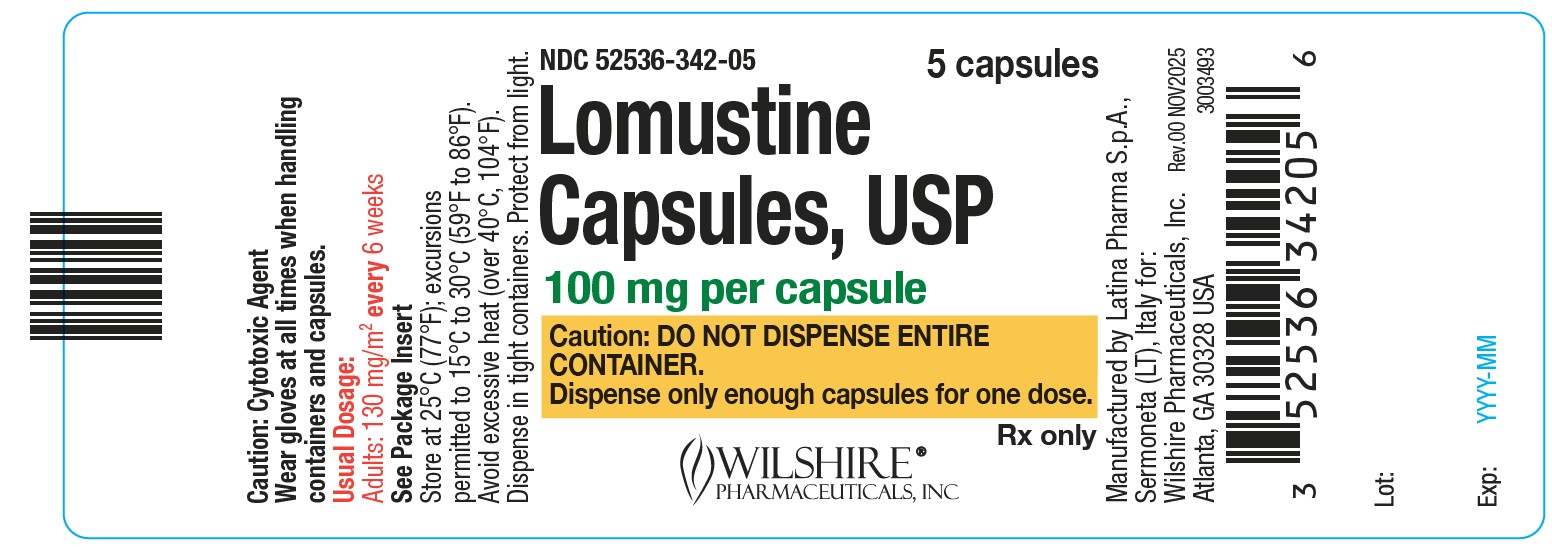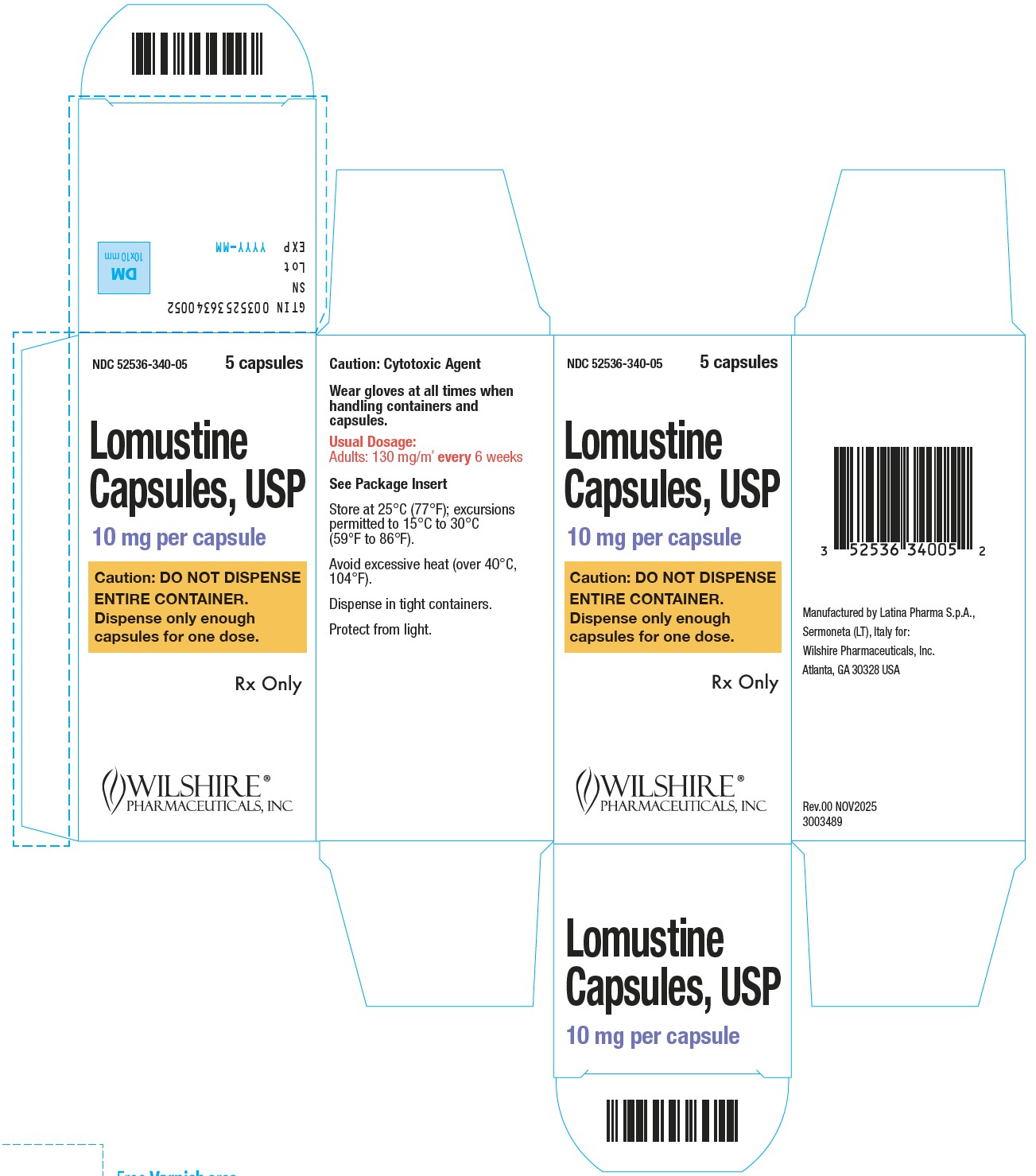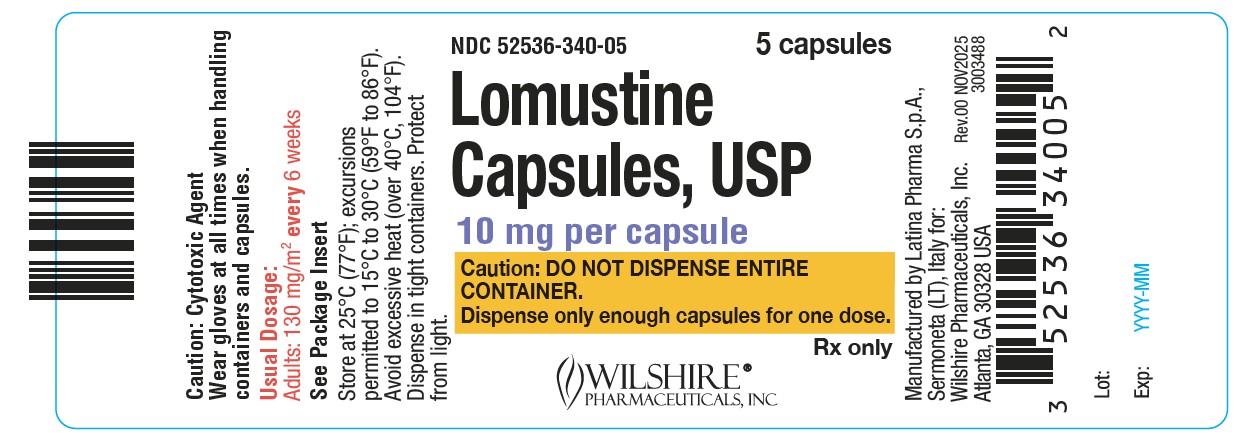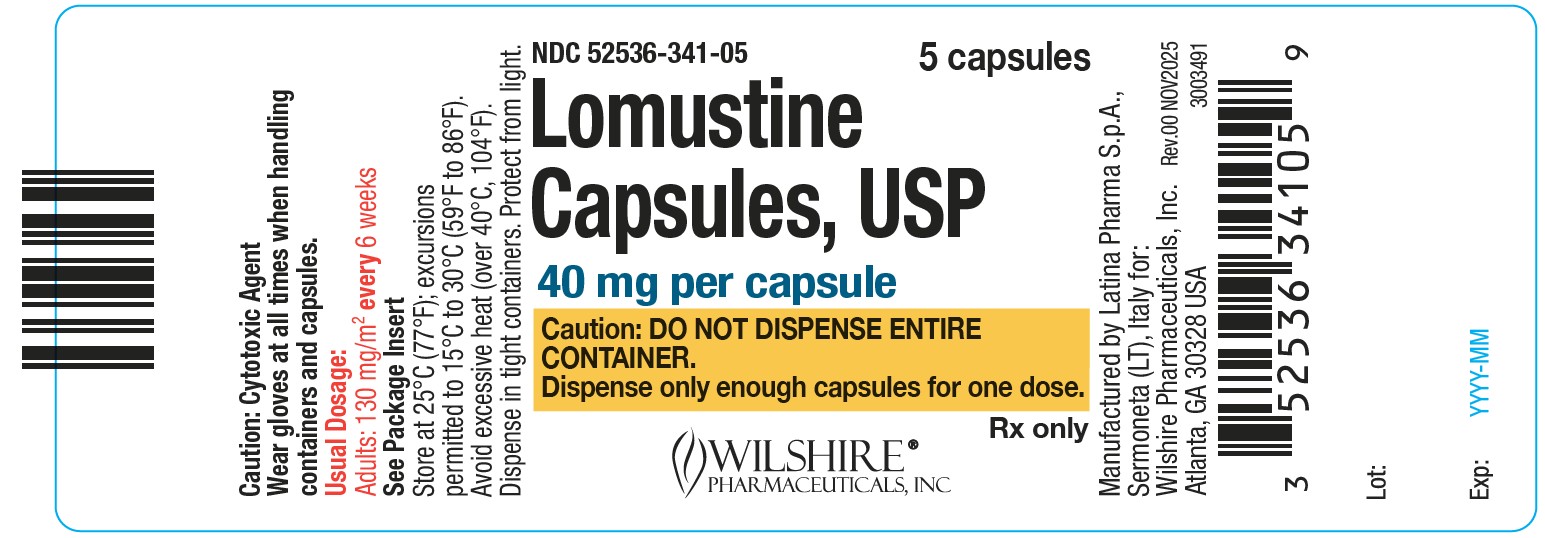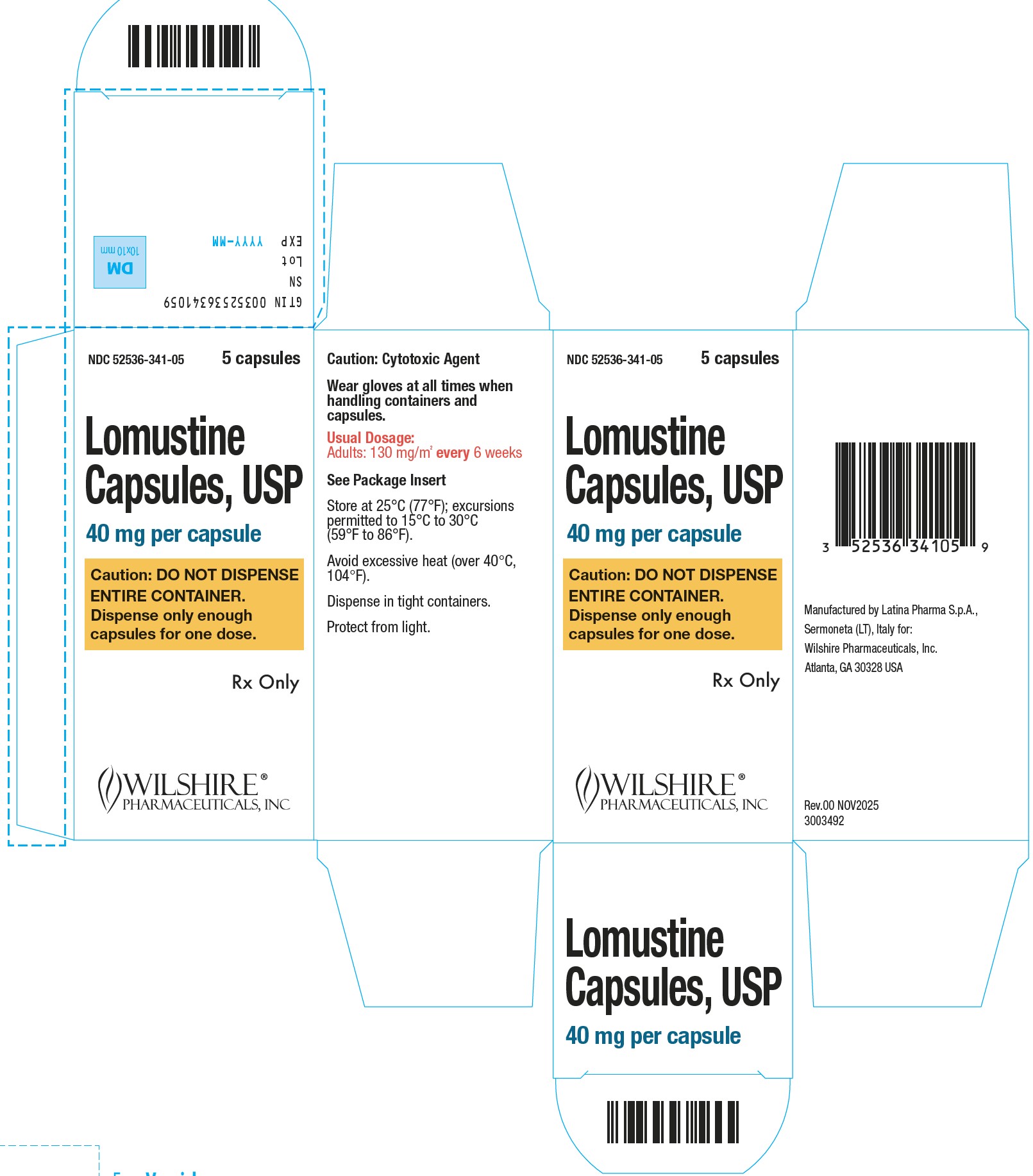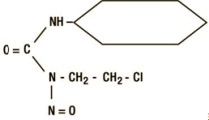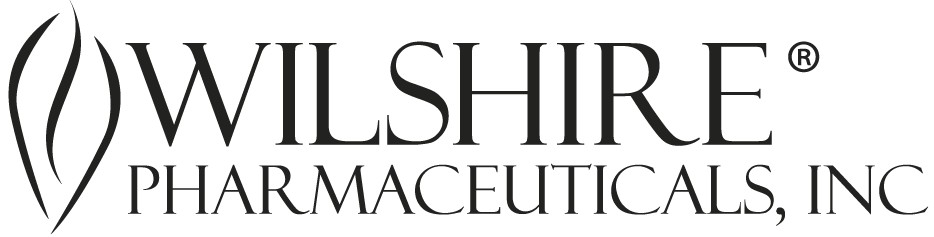 DRUG LABEL: Lomustine
NDC: 52536-341 | Form: CAPSULE, GELATIN COATED
Manufacturer: Wilshire Pharmaceuticals, Inc.
Category: prescription | Type: Human Prescription Drug Label
Date: 20251130

ACTIVE INGREDIENTS: LOMUSTINE 40 mg/1 1
INACTIVE INGREDIENTS: MAGNESIUM STEARATE; MANNITOL

HIGHLIGHTS OF PRESCRIBING INFORMATION

These highlights do not include all the information needed to use LOMUSTINE CAPSULES safely and effectively. See full prescribing information for LOMUSTINE CAPSULES.
LOMUSTINE capsules, for oral use
Initial U.S. Approval: 1976

WARNING: DELAYED MYELOSUPPRESSION and RISK OF OVERDOSAGE

See full prescribing information for complete boxed warning.
Delayed Myelosuppression
Lomustine causes myelosuppression including fatal myelosuppression. Myelosuppression is delayed, dose-related, and cumulative. Thrombocytopenia is generally more severe than leukopenia. Monitor blood counts and do not give lomustine more frequently than every 6 weeks. (2.2, 2.3, 5.1)
Risk of Overdosage
PRESCRIBE, DISPENSE, AND ADMINISTER ONLY ENOUGH CAPSULES FOR ONE DOSE. Fatal toxicity occurs with overdosage of lomustine. Both physician and pharmacist should emphasize to patient that only one dose of lomustine is taken every 6 weeks. (2.1, 5.2, 10)

1 INDICATIONS AND USAGE

Lomustine is an alkylating drug indicated for the treatment of patients with:

- Brain tumors, primary and metastatic, following appropriate surgical and/or radiotherapeutic procedures. (1)
- Hodgkin's lymphoma in combination with other chemotherapies, following disease progression with initial chemotherapy. (1)

2 DOSAGE AND ADMINISTRATION

- Recommended dose in adult and pediatric patients is 130 mg/m^2 orally every 6 weeks. (2.1)
- Round dose to nearest 10 mg.
- Give as a single oral dose and do not repeat for at least 6 weeks.

3 DOSAGE FORMS AND STRENGTHS

Capsules: 10 mg, 40 mg, and 100 mg (3)

5 WARNINGS AND PRECAUTIONS

- Pulmonary toxicity: Pulmonary infiltrates and/or fibrosis occurs with lomustine. Perform pulmonary function tests prior to treatment and repeat frequently. Permanently discontinue lomustine in patients diagnosed with pulmonary fibrosis. (5.3)
- Secondary malignancies: Acute leukemia and myelodysplasia can occur with long-term use. (5.4)
- Hepatotoxicity: Increased levels of transaminases, alkaline phosphatase and bilirubin can occur with lomustine. Monitor liver function. (5.5)
- Nephrotoxicity: Can cause renal failure. Monitor renal function. (5.6)
- Embryo-fetal toxicity: Can cause fetal harm. Advise males and females of reproductive potential of the potential risk to a fetus and to use effective contraception. (5.7, 8.1, 8.3)

6 ADVERSE REACTIONS

Common adverse reactions include delayed myelosupression, nausea, vomiting, stomatitis, and alopecia. (6)

To report SUSPECTED ADVERSE REACTIONS, contact Wilshire Pharmaceuticals, Inc. at 1-800-461-7449 or FDA at 1-800-FDA-1088 or www.fda.gov/medwatch.

8 USE IN SPECIFIC POPULATIONS

Lactation: Do not breastfeed. (8.2)

FULL PRESCRIBING INFORMATION

WARNING: DELAYED MYELOSUPPRESSION and RISK OF OVERDOSAGE

DELAYED MYELOSUPPRESSION
Lomustine causes myelosuppression including fatal myelosuppression. Myelosuppression is delayed, dose-related, and cumulative; occurring 4 to 6 weeks after drug administration and persisting for 1 to 2 weeks. Thrombocytopenia is generally more severe than leukopenia. Cumulative myelosuppression from lomustine is manifested by greater severity and longer duration of cytopenias. Monitor blood counts for at least 6 weeks after each dose. Do not give lomustine more frequently than every 6 weeks [see Warnings and Precautions (5.1), Dosage and Administration (2.2, 2.3)].
RISK OF OVERDOSAGE
PRESCRIBE, DISPENSE, AND ADMINISTER ONLY ENOUGH CAPSULES FOR ONE DOSE. Fatal toxicity occurs with overdosage of lomustine. Both physician and pharmacist should emphasize to the patient that only one dose of lomustine is taken every 6 weeks [see Dosage and Administration (2.1), Warnings and Precautions (5.2), Overdosage (10)].

1 INDICATIONS AND USAGE

1.1 Brain Tumors

Lomustine is indicated for the treatment of patients with primary and metastatic brain tumors following appropriate surgical and/or radiotherapeutic procedures.

1.2 Hodgkin's Lymphoma

Lomustine is indicated as a component of combination chemotherapy for the treatment of patients with Hodgkin's lymphoma whose disease has progressed following initial chemotherapy.

2 DOSAGE AND ADMINISTRATION

2.1 Important Prescribing and Dispensing Information

PRESCRIBE ONLY ONE DOSE FOR EACH TREATMENT CYCLE. DO NOT DISPENSE ENTIRE CONTAINER. Dispense only a sufficient number of capsules for one dose.

Confirm the total dose prescribed by the physician and the appropriate combination of capsule strengths.

Dispense only the appropriate number of lomustine capsules required for the administration of a single dose.

The prescribed dose may consist of two or more different strengths and colors of capsules.

Instruct patients that lomustine is taken as a single oral dose and will not be repeated for at least 6 weeks. Taking more than the recommended dose causes toxicities, including fatal outcomes [see Warnings and Precautions (5.2) and Overdosage (10)].

Lomustine is a cytotoxic drug. Follow applicable special handling and disposal procedures.^1

To minimize the risk of dermal exposure, always wear impervious gloves when handling bottles containing lomustine capsules. Do not break lomustine capsules; avoid exposure to broken capsules. If dermal contact occurs, wash areas of skin contact immediately and thoroughly.

2.2 Recommended Dose

The recommended dose of lomustine in adult and pediatric patients is 130 mg/m^2 taken as a single oral dose every 6 weeks. Round doses to the nearest 10 mg. Give as a single oral dose and do not repeat for at least 6 weeks. Reduce dose to 100 mg/m^2 every 6 weeks in patients with compromised bone marrow function. Also reduce dose accordingly when using with other myelosuppressive drugs.

2.3 Dose Modifications

Perform weekly complete blood counts and withhold each subsequent dose for more than 6 weeks if needed until platelet counts recover to 100,000/mm^3 or greater and leukocytes recover to 4000/mm^3 or greater [see Warnings and Precautions (5.1)].

Modify each dose of lomustine according to the hematologic response of the preceding dose as described in Table 1:

Table 1. Dose Modifications for Lomustine
Nadir After Prior Dose |  | Dose Adjustment
Leukocytes (/mm^3) | Platelets (/mm^3) | Dose Adjustment
≥ 4000 | ≥ 100,000 | None
3000 – 3999 | 75,000 – 99,999 | None
2000 – 2999 | 25,000 – 74,999 | Reduce dose by 30%
< 2000 | < 25,000 | Reduce dose by 50%

3 DOSAGE FORMS AND STRENGTHS

Lomustine Capsules, USP are available in three strengths, distinguishable by the color of the capsules:

- 100 mg capsules (green/green)
- 40 mg capsules (white/green)
- 10 mg capsules (white/white)

4 CONTRAINDICATIONS

None.

5 WARNINGS AND PRECAUTIONS

5.1 Delayed Myelosuppression

Lomustine causes myelosuppression that can result in fatal infections and bleeding. Myelosuppression from lomustine is delayed, dose-related, and cumulative. It usually occurs 4 to 6 weeks after drug administration and persists for 1 to 2 weeks. Thrombocytopenia is generally more severe than leukopenia. Cumulative myelosuppression from lomustine is manifested by greater severity and longer duration of cytopenias.

Monitor blood counts for at least 6 weeks after each dose. Do not give lomustine more frequently than every 6 weeks. Adjust dose based on nadir blood counts from prior dose [see Dosage and Administration (2.3)].

5.2 Risk of Overdosage

Fatal toxicity occurs with overdosage of lomustine. Dispensing or administering more than one dose can lead to fatal toxicity.

Prescribe only one dose at a time. Dispense only enough capsules for one dose. Both physician and pharmacist should emphasize to the patient that only one dose of lomustine is taken every 6 weeks [see Dosage and Administration (2.1) and Overdosage (10)].

5.3 Pulmonary Toxicity

Pulmonary toxicity characterized by pulmonary infiltrates and/or fibrosis occurs with lomustine. Patients with a baseline below 70% of the predicted Forced Vital Capacity (FVC) or Carbon Monoxide Diffusing Capacity (DLCO) are at increased risk. The onset of pulmonary toxicity occurs after an interval of 6 months or longer from the start of therapy, with cumulative doses of lomustine usually greater than 1100 mg/m^2.

Obtain baseline pulmonary function tests prior to initiating treatment and repeat frequently during treatment. Permanently discontinue lomustine in patients diagnosed with pulmonary fibrosis.

5.4 Secondary Malignancies

Secondary malignancies, including acute leukemia and myelodysplasia, occur with long term use.

5.5 Hepatotoxicity

Hepatic toxicity, manifested by increased levels of transaminases, alkaline phosphatase, and bilirubin occurs with lomustine.

Monitor liver function.

5.6 Nephrotoxicity

Progressive renal failure with a decrease in kidney size occurs with lomustine.

Monitor renal function.

5.7 Embryo-Fetal Toxicity

Based on animal data and its mechanism of action, lomustine can cause fetal harm when administered to a pregnant woman. Embryo-fetal toxicity and teratogenicity occurred in rats and rabbits receiving lomustine daily during organogenesis at doses approximately two to four times the total human dose of 130 mg/m^2 over 6 weeks (0.18 to 0.27 times the single human dose of 130 mg/m^2) based on body surface area (BSA). Advise pregnant women of the potential risk to a fetus. Advise females of reproductive potential to use effective contraception during treatment with lomustine and for 2 weeks after the final dose. Advise males with female partners of reproductive potential to use effective contraception during treatment with lomustine and for 3.5 months after the final dose [see Use in Specific Populations (8.1, 8.3)].

6 ADVERSE REACTIONS

The following serious adverse reactions are discussed in greater detail in other sections of the labeling:

- Delayed myelosuppression [see Warnings and Precautions (5.1)]
- Risks of overdosage [see Warnings and Precautions (5.2)]
- Pulmonary toxicity [see Warnings and Precautions (5.3)]
- Secondary malignancies [see Warnings and Precautions (5.4)]
- Hepatotoxicity [see Warnings and Precautions (5.5)]
- Nephrotoxicity [see Warnings and Precautions (5.6)]

The following adverse reactions associated with the use of lomustine were identified in clinical trials or postmarketing reports. Because these reactions were reported from a population of uncertain size, it is not possible to estimate their frequency, reliability, or establish a causal relationship to drug exposure.

Gastrointestinal disorders: nausea, vomiting, and stomatitis

Ocular disorders: optic atrophy, visual disturbances, and blindness

Neurologic disorders: disorientation, lethargy, ataxia, and dysarthria

Other: alopecia

8 USE IN SPECIFIC POPULATIONS

8.1 Pregnancy

Risk Summary
Based on animal data and its mechanism of action, lomustine can cause fetal harm when administered to a pregnant woman [see Clinical Pharmacology (12.1)]. There are no available data on lomustine exposure in pregnant women. Lomustine was teratogenic in rats and embryotoxic in rabbits at total dose levels approximately two to four times the total human dose of 130 mg/m^2 over 6 weeks (0.18 to 0.27 times the single human dose of 130 mg/m^2) based on BSA [see Data]. Advise pregnant women of the potential risk to a fetus.
In the U.S. general population, the estimated background risk of major birth defects and miscarriage in clinically recognized pregnancies is 2-4% and 15-20%, respectively.
Data
Animal Data
Lomustine was administered by intraperitoneal injection daily to pregnant rats during the period of organogenesis at dose levels of 0, 2, 4, 6, and 8 mg/kg. Resorption rates and post-implantation loss occurred at doses greater than or equal to 4 mg/kg (approximately 0.18 times the clinical dose of 130 mg/m^2 based on BSA or approximately twice the total clinical dose of lomustine over 6 weeks). Malformations (omphalocele, ectopia cordis, scoliosis, syndactyly, hydrocephalus, microphthalmia, anophthalmia, anomalies of aortic arch, dextrocardia, malpositioning of the ovaries and testes, sternoschisis, and shortened/misshapen bone of the fore or hind limbs) and decreased fetal body weight occurred at all dose levels. In pregnant rabbits treated with lomustine at 3 mg/kg (approximately 0.27 times the 130 mg/m^2 clinical dose based on BSA or approximately four times the total clinical dose of lomustine over 6 weeks) during organogenesis, there were increases in abortions and decreases in surviving pup weight that persisted postnatally.

8.2 Lactation

Risk Summary
There is no information on the presence of lomustine or its metabolites in human milk, its effects on the breastfed infant, or its effects on milk production. Because of the potential for serious adverse reactions in breastfed infants from lomustine, advise women not to breastfeed during treatment with lomustine and for 2 weeks after the final dose.

8.3 Females and Males of Reproductive Potential

Contraception
Females
Based on animal data and its mechanism of action, lomustine can cause fetal harm [see Use in Specific Populations (8.1)]. Advise females of reproductive potential to use effective contraception during treatment and for 2 weeks after the final dose.
Males
Based on lomustine’s mechanism of action, advise males with female partners of reproductive potential to use effective contraception during treatment with lomustine and for 3.5 months after the final dose [see Clinical Pharmacology (12.1)].
Infertility
Based on animal findings and its mechanism of action, lomustine may result in reduced fertility in males and females of reproductive potential [see Nonclinical Toxicology (13.1)].

8.4 Pediatric Use

Pediatric use, including dose, is not based on adequate and well-controlled clinical studies.

8.5 Geriatric Use

No data in the clinical studies of lomustine are available for patients 65 years of age and over to determine whether they respond differently than younger patients. Other reported clinical experience has not identified differences in responses between elderly and younger patients. In general, dose selection for an elderly patient should be cautious, reflecting the greater frequency of decreased hepatic, renal, or cardiac function and of concomitant disease or other drug therapy.

Lomustine and its metabolites are known to be substantially excreted by the kidney, and the risk of toxic reactions to this drug may be greater in patients with impaired renal function. Because elderly patients are more likely to have decreased renal function, care should be taken in dose selection, and renal function should be monitored.

10 OVERDOSAGE

Overdosage with lomustine has occurred, including fatal cases [see Dosage and Administration (2.1), Warnings and Precautions (5.2)]. Overdosage causes severe myelosuppression, as well as abdominal pain, diarrhea, vomiting, anorexia, lethargy, dizziness, abnormal hepatic function, cough, and shortness of breath.

No antidotes exist for lomustine overdosage.

11 DESCRIPTION

Lomustine is an alkylating drug for oral administration. The chemical name for lomustine is 1-(2-chloro-ethyl)-3-cyclohexyl-1-nitrosourea and the molecular formula is C9H16ClN3O2. The molecular weight is 233.71. Lomustine is a yellow powder, which is soluble in 10% ethanol (0.05 mg per mL) and in absolute alcohol (70 mg per mL). Lomustine is insoluble in water (<0.05 mg per mL).

The chemical structure is:

Lomustine Capsules, USP are supplied as 10 mg, 40 mg, and 100 mg capsules and contains the following inactive ingredients: magnesium stearate NF and mannitol USP. The capsule shells are composed of gelatin and coloring pigments, depending on the strength: titanium dioxide, and/or yellow iron oxide, and/or Indigotine – FD&C Blue2.

12 CLINICAL PHARMACOLOGY

12.1 Mechanism of Action

Lomustine alkylates DNA and RNA. As with other nitrosoureas, it may also inhibit several key enzymatic processes by carbamoylation of amino acids in proteins.

12.2 Pharmacodynamics

The pharmacodynamics of lomustine are unknown.

12.3 Pharmacokinetics

Distribution
Lomustine crosses the blood-brain barrier.
Elimination
The serum half-life of lomustine metabolites ranges from 16 hours to 48 hours.
Metabolism
Metabolic pathways involved in the elimination of lomustine have not been characterized.
Excretion
Following oral administration of radioactive lomustine at doses ranging from 30 mg/m^2 to 100 mg/m^2, approximately half of the radioactivity administered was excreted in the urine in the form of degradation products within 24 hours.
Specific Populations
The impact of patient specific (e.g., age, sex, and race) or disease (e.g., renal or hepatic impairment) characteristics on the pharmacokinetics of lomustine is unknown.

13 NONCLINICAL TOXICOLOGY

13.1 Carcinogenesis, Mutagenesis, Impairment of Fertility

Lomustine is carcinogenic in rats and mice, producing a marked increase in tumor incidence in doses lower than those employed clinically.

In female rats, daily intraperitoneal treatment with lomustine for 2 weeks prior to mating with untreated males resulted in dose dependent decreases in number of corpora lutea and resorption rates with no live births at a dose of 3 mg/kg (approximately 0.14 times the recommended clinical dose of 130 mg/m^2 based on body surface area (BSA), or approximately twice the total clinical dose of lomustine over 6 weeks) and decreased pup survival during the first 4 postnatal days at doses greater than or equal to 1.5 mg/kg (a daily dose of approximately 0.06 times the recommended clinical dose of 130 mg/m^2 based on BSA or approximately equal to the total clinical dose of lomustine over 6 weeks). Lomustine may also result in decreased male fertility. Intraperitoneal injection of lomustine resulted in decreased fertility in male rats mated to untreated females based on decreased implantations and decreased fetal body weight at weekly doses greater than or equal to 5 mg/kg (approximately 0.23 times the single clinical dose of 130 mg/m^2 based on BSA, or approximately equal to the total clinical dose of lomustine over 6 weeks), and increased resorptions at doses greater than or equal to 2.5 mg/kg/week.

15 REFERENCES

OSHA. http://www.osha.gov/SLTC/hazardousdrugs/index.html.

16 HOW SUPPLIED/STORAGE AND HANDLING

16.1 How Supplied

Lomustine Capsules, USP are available in three strengths, distinguishable by the color of the capsules, in individual bottles of 5 capsules each:

Strength | Capsule Description | NDC Code
100 mg | Moss green cap and body, imprinted in black ink, with "CPL" over "3032" on the cap and "100 mg" on the body of the capsule. | 52536-342-05
40 mg | White cap and a moss green body, imprinted in black ink, with "CPL" over "3031" on the cap and "40 mg" on the body of the capsule. | 52536-341-05
10 mg | White cap and body, imprinted in black ink, with "CPL" over "3030" on the cap and "10 mg" on the body of the capsule | 52536-340-05

16.2 Storage and Handling

Store at 25°C (77°F); excursions permitted to 15°C to 30°C (59°F to 86°F) [see USP Controlled Room Temperature]. Avoid temperatures over 40°C (104°F).

Lomustine is a cytotoxic drug. Follow applicable special handling and disposal procedures.^1

To minimize the risk of dermal exposure, always wear impervious gloves when handling bottles containing lomustine capsules. Do not break lomustine capsules; avoid exposure to broken capsules. If dermal contact occurs, wash areas of skin contact immediately and thoroughly.

17 PATIENT COUNSELING INFORMATION

Myelosuppression
Advise patients that periodic assessment of their blood counts are required. Advise patients to contact their healthcare provider for new onset of bleeding or fever or symptoms of infection [see Warnings and Precautions (5.1)].
Overdosage
Advise patients that toxicity including fatal toxicity occurs with lomustine overdosage [see Warnings and Precautions (5.2), Overdosage (10), Dosage and Administration (2.1)].
Advise patients to take lomustine as directed:

- Lomustine is taken as a single oral dose that will not be repeated for at least 6 weeks.
- Use of the recommended dose at less than 6 week intervals leads to toxicities including fatal toxicities.
- Each dose may consist of 2 or more different strengths and colors of capsules.

Pulmonary Fibrosis
Advise patients to contact their healthcare provider for new or worsening cough, chest pain, or shortness of breath [see Warnings and Precautions (5.3)].
Hepatotoxicity
Inform patients that lomustine can cause hepatotoxicity and that liver function monitoring during treatment is necessary [see Warnings and Precautions (5.5)].
Nephrotoxicity
Inform patients that lomustine can cause nephrotoxicity and that renal function and electrolyte monitoring during treatment is necessary [see Warnings and Precautions (5.6)].
Embryo-Fetal Toxicity
Advise females of reproductive potential of the potential risk to a fetus and to inform their healthcare provider of a known or suspected pregnancy [see Warnings and Precautions (5.7), Use in Specific Populations (8.1)].
Advise females of reproductive potential to use effective contraception during treatment with lomustine and for at least 2 weeks after the final dose [see Use in Specific Populations (8.3)].
Advise male patients with female partners of reproductive potential to use condoms during treatment with lomustine and for 3.5 months after the final dose [see Use in Specific Populations (8.3)].
Lactation
Advise women not to breastfeed during treatment with lomustine and for 2 weeks after the final dose [see Use in Specific Populations (8.2)].
Infertility
Advise females and males of reproductive potential of the potential for reduced fertility from lomustine [see Use in Specific Populations (8.3) and Nonclinical Toxicology (13.1)].

Manufactured by Latina Pharma S.p.A., Sermoneta (LT), Italy for:
Wilshire Pharmaceuticals, Inc.
Atlanta, GA 30328 USA
Rev.00 NOV2025

Principal Display Panel - Carton Label

NDC 52536-342-05 5 capsules

Lomustine Capsules, USP

100 mg per capsule

Caution: DO NOT DISPENSE
ENTIRE CONTAINER.
Dispense only enough
capsules for one dose.

Rx Only

Wilshire Pharmaceuticals, Inc.

Principal Display Panel - Label

NDC 52536-342-05 5 capsules

Lomustine Capsules, USP

100 mg per capsule

Caution: DO NOT DISPENSE
ENTIRE CONTAINER.
Dispense only enough
capsules for one dose.

Rx Only

Wilshire Pharmaceuticals, Inc.

Principal Display Panel - Carton Label

NDC 52536-341-05 5 capsules

Lomustine Capsules, USP

40 mg per capsule

Caution: DO NOT DISPENSE
ENTIRE CONTAINER.
Dispense only enough
capsules for one dose.

Rx Only

Wilshire Pharmaceuticals, Inc.

Principal Display Panel - Label

NDC 52536-341-05 5 capsules

Lomustine Capsules, USP

40 mg per capsule

Caution: DO NOT DISPENSE
ENTIRE CONTAINER.
Dispense only enough
capsules for one dose.

Rx Only

Wilshire Pharmaceuticals, Inc.

Principal Display Panel - Carton Label

NDC 52536-340-05 5 capsules

Lomustine Capsules, USP

10 mg per capsule

Caution: DO NOT DISPENSE
ENTIRE CONTAINER.
Dispense only enough
capsules for one dose.

Rx Only

Wilshire Pharmaceuticals, Inc.

Principal Display Panel - Label

NDC 52536-340-05 5 capsules

Lomustine Capsules, USP

10 mg per capsule

Caution: DO NOT DISPENSE
ENTIRE CONTAINER.
Dispense only enough
capsules for one dose.

Rx Only

Wilshire Pharmaceuticals, Inc.